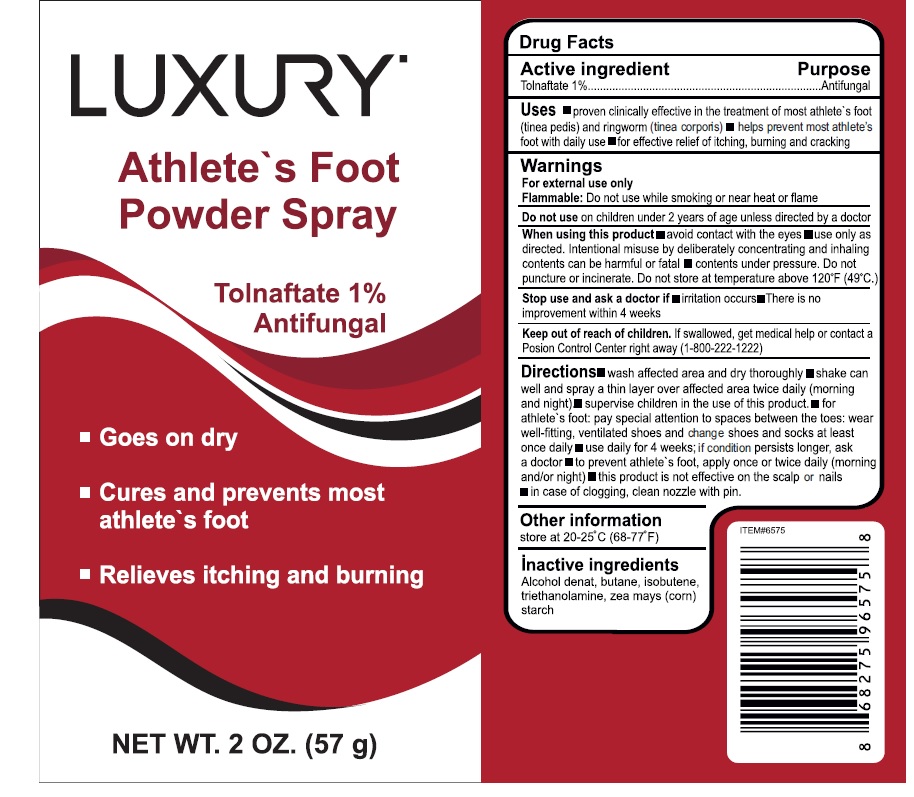 DRUG LABEL: Luxury
NDC: 76772-022 | Form: AEROSOL, SPRAY
Manufacturer: TSM ITHALAT IHRACAT SANAYI VE DIS TICARET LIMITED SIRKETI
Category: otc | Type: HUMAN OTC DRUG LABEL
Date: 20210310

ACTIVE INGREDIENTS: TOLNAFTATE 1.3 g/57 g
INACTIVE INGREDIENTS: BUTANE; ISOBUTYLENE; TROLAMINE; STARCH, CORN; ALCOHOL

LUXURY Athlete's Foot Powder Spray

Active Ingredient

Tolnaftate 1%

Purpose

Antifungal

Uses

- proven clinically effective in the treatment of most athlete's foot (tinea pedis) and ringworm (tinea corporis)
- helps prevents most athlete's foot with daily use
- for effective relief of itching, cracking and burning

Warnings

For external use only.

Extremely flammable:

Do not use while smoking or near heat or flame

When using this product

- avoid contact with the eyes
- use only as directed. intentional misuse by deliberately concentrating and inhaling contents can be harmful or fatal
- contents under pressure. Do not puncture or incinerate. Do not store temperature above 120 F (49 C)

Stop use and ask a doctor if

- irritation occurs
- There is no improvement within 4 weeks

Do not use

on children under 2 years of age unless directed by a doctor.

Keep out of reach of children.

If swallowed, get medical help or contact a Poison Control Center right away.

Directions

- shake can well and spray a thin layer over affected area twice daily (morning and night)
- wash affected area and dry thoroughly
- hold can 4-6 inches away from affected area
- supervise children in the use of this product
- for athlete's foot, pay special attention to spaces between the toes; wear well-fitting, ventilated shoes, and change shoes and socks at least once daily
- use daily for 4 weeks; if condition persists longer, ask a doctor
- if condition persists longer, consult a doctor
- this product is not effective on the scalp or nails
- in case of clogging , clean nozzle with a pin

Other information

- store between 20° and 25°C (68° and 77°F)

Inactive ingredients

Alcohol denat, Butane , Isobutene , Triethanolamine , zea mays (corn) starch.